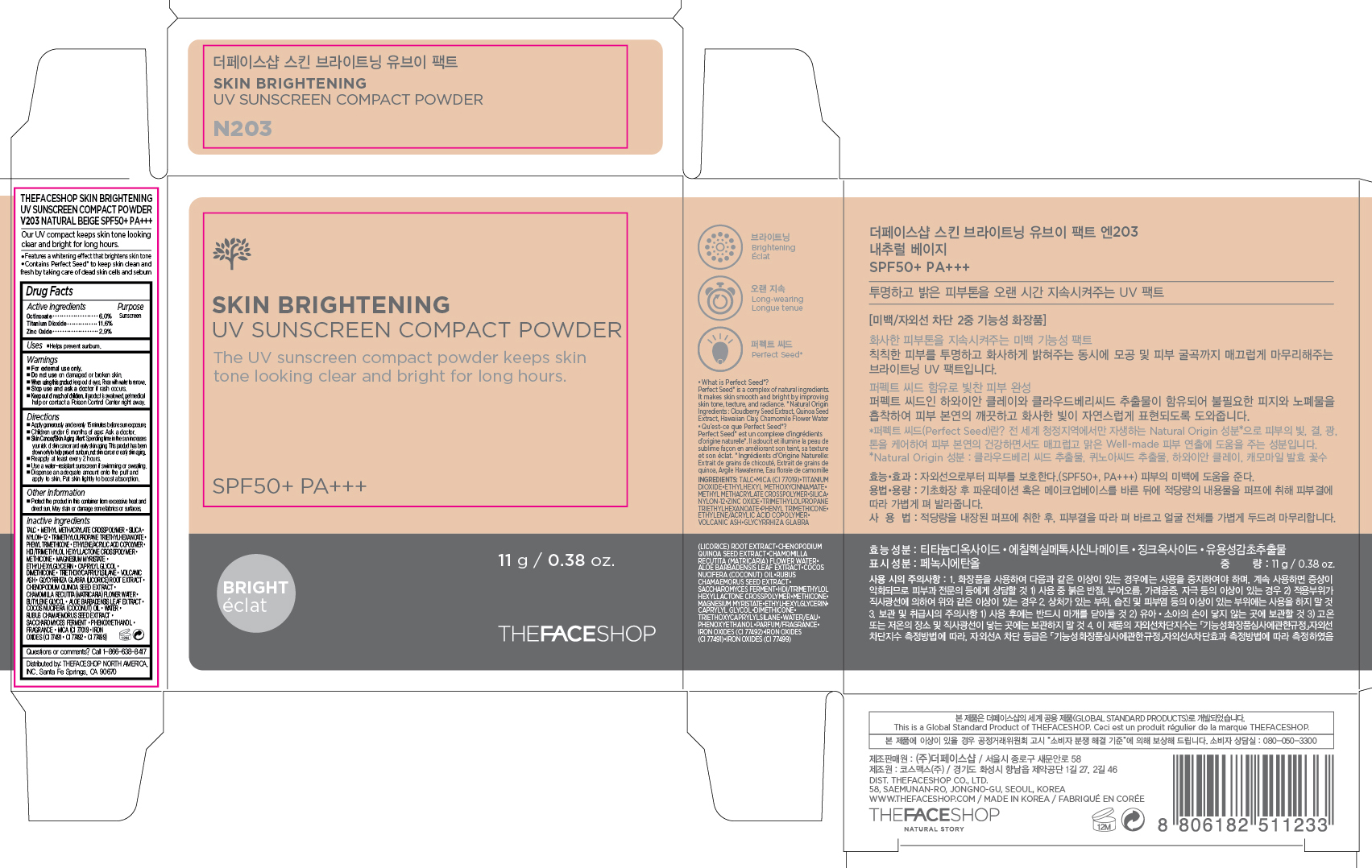 DRUG LABEL: SKIN BRIGHTENING
NDC: 51523-373 | Form: POWDER
Manufacturer: THEFACESHOP CO., LTD.
Category: otc | Type: HUMAN OTC DRUG LABEL
Date: 20150925

ACTIVE INGREDIENTS: OCTINOXATE 0.66 g/11 g; TITANIUM DIOXIDE 1.28 g/11 g; ZINC OXIDE 0.32 g/11 g
INACTIVE INGREDIENTS: WATER

SKIN BRIGHTENING UV SUNSCREEN COMPACT POWDER V203 NATURAL BEIGE 34200373

Active Ingredients

Octinoxate 6.0 %

Titanium Dioxide 11.6 %

Zinc Oxide 2.9 %

Purpose

Sunscreen

Sunscreen

Sunscreen

Uses

Helps prevent sunburn.

Warnings

For external use only.

Do not use on damaged or broken skin

When using this product keep out of eyes. Rinse with water to remove.

Stop use and ask a doctor if rash occurs.

Keep out of reach of children. If product is swallowed, get medical help or contact a Poison Control Center right away.

Directions

Apply generously and evenly 15 minutes before sun exposure.
Children under 6 months of age: Ask a doctor.
Skin Cancer/Skin Aging Alert: Spending time in the sun increases your risk of skin cancer and early skin aging. This product has been shown only to help prevent sunburn, not skin cancer or early skin aging.
Reapply at least every 2 hours.
Use a water-resistant sunscreen if swimming or sweating.

Dispense an adequate amount onto the puff and apply to skin. Pat skin lightly to boost absorption.

OTHER SAFETY INFORMATION

Protect the product in this container from excessive heat and direct sun.

May stain or damage some fabrics or surfaces.

Inactive Ingredients

Talc, Methyl Methacrylate Crosspolymer, Silica, Nylon-12, Trimethylolpropane Triethylhexanoate, Phenyl Trimethicone, Ethylene/Acrylic Acid Copolymer, HDI/Trimethylol Hexyllactone Crosspolymer, Methicone, Magnesium Myristate, Ethylhexylglycerin, Caprylyl Glycol, Dimethicone, Triethoxycaprylylsilane, Volcanic Ash, Glycyrrhiza Glabra (Licorice) Root Extract, Chenopodium Quinoa Seed Extract, Chamomilla Recutita (Matricaria) Flower Water, Butylene Glycol, Aloe Barbadensis Leaf Extract, Cocos Nucifera (Coconut) Oil, Water, Rubus Chamaemorus Seed Extract, Saccharomyces Ferment, Phenoxyethanol, Fragrance, Mica (CI 77019), Iron Oxides (CI 77491, CI 77492, CI 77499)

Questions or comments? Call 1-866-638-8417

Distributed by:

THEFACESHOP NORTH AMERICA, INC.

Santa Fe Springs, CA 90670

PACKAGE LABEL

SKIN BRIGHTENING

UV SUNSCREEN COMPACT POWDER

V203 NATURAL BEIGE SPF 50+ PA+++

Our UV compact keeps skin tone looking clear and bright for long hours.

Features a whitening effect that brightens skin tone.

Contains Perfect Seed to keep skin clean and fresh by taking care of dead skin cells and sebum.